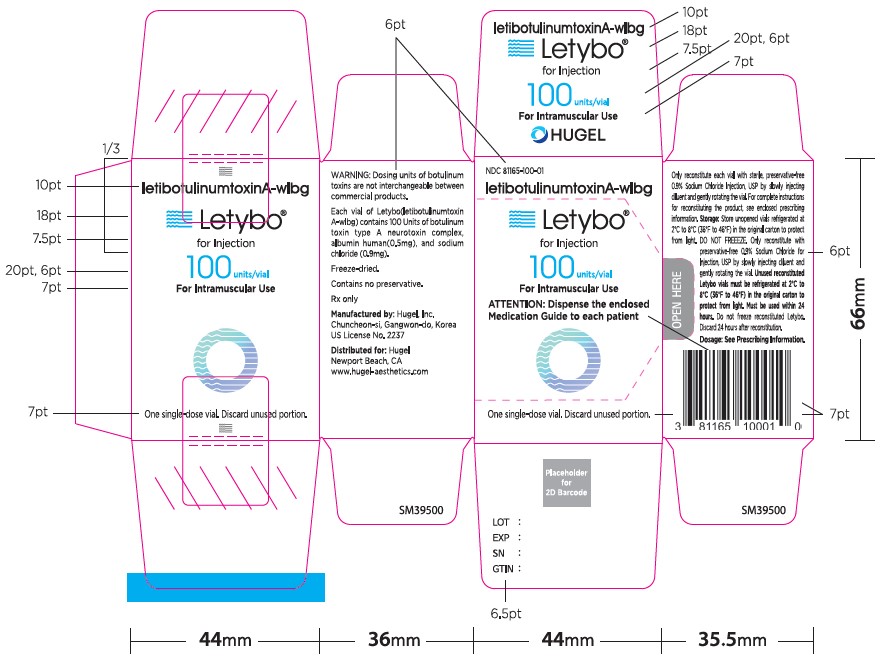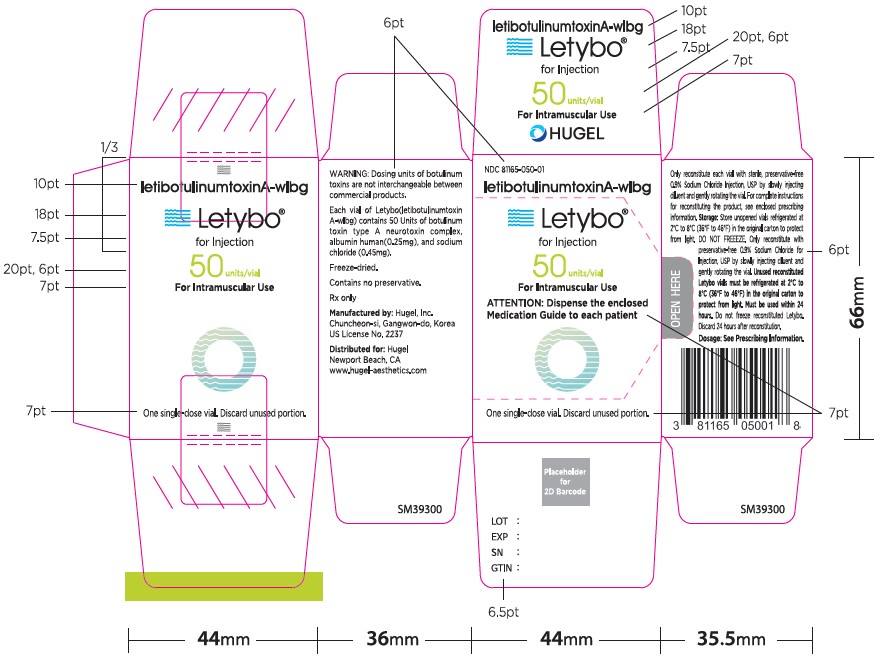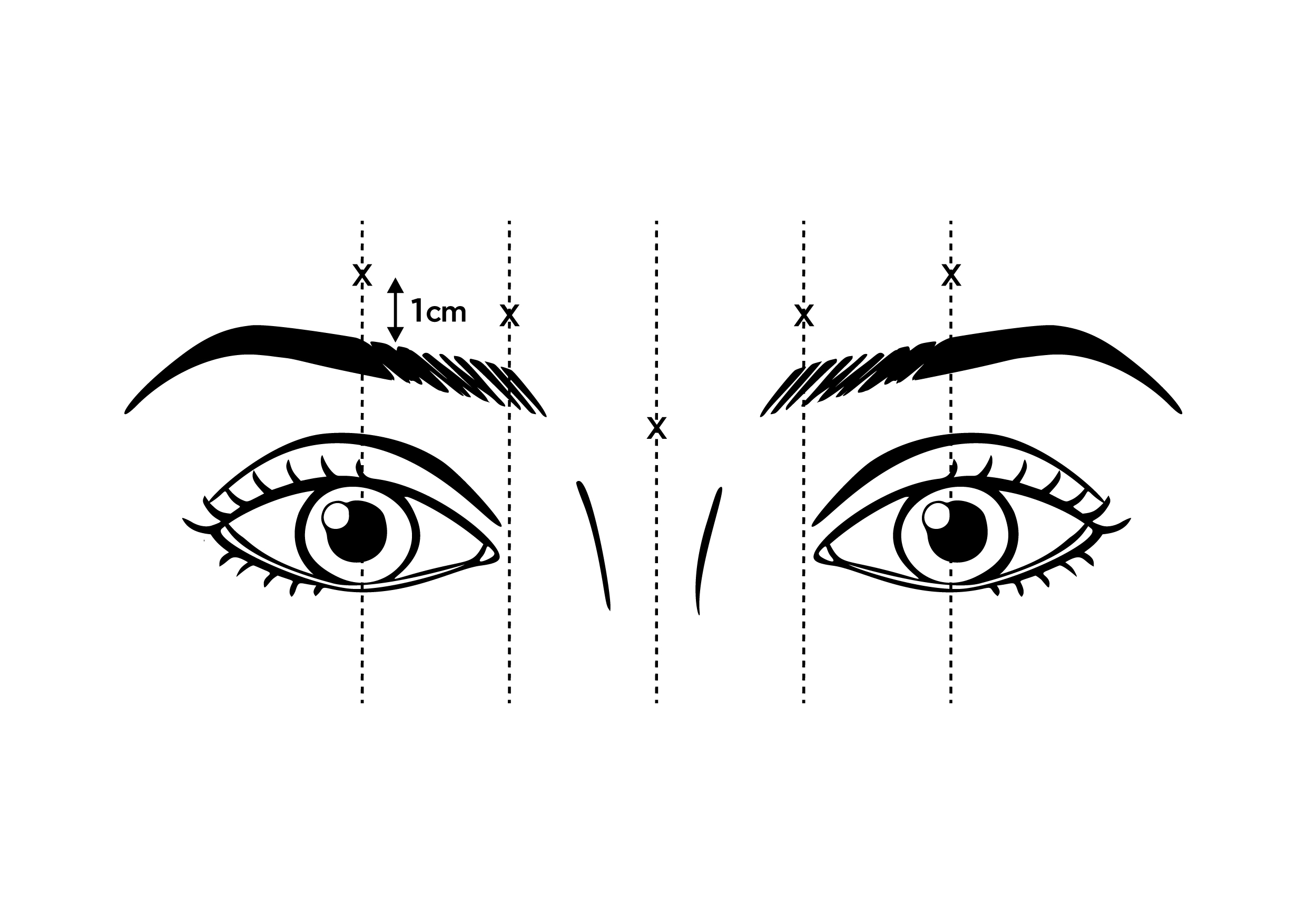 DRUG LABEL: LETYBO
NDC: 81165-050 | Form: INJECTION, POWDER, LYOPHILIZED, FOR SOLUTION
Manufacturer: Hugel, Inc.
Category: prescription | Type: HUMAN PRESCRIPTION DRUG LABEL
Date: 20241118

ACTIVE INGREDIENTS: LETIBOTULINUMTOXINA 50 U/1 1

HIGHLIGHTS OF PRESCRIBING INFORMATION

These highlights do not include all the information needed to use LETYBO safely and effectively. See full prescribing information for LETYBO.
LETYBO (letibotulinumtoxinA-wlbg) for injection, for intramuscular use
Initial U.S. Approval: 2024

WARNING: DISTANT SPREAD OF TOXIN EFFECT

See full prescribing information for complete boxed warning.

The effects of all botulinum toxin products, including LETYBO, may spread from the area of injection to produce symptoms consistent with botulinum toxin effects. These symptoms have been reported hours to weeks after injection. Swallowing and breathing difficulties can be life threatening and there have been reports of death.

LETYBO is not approved for the treatment of spasticity or any conditions other than glabellar lines. (5.1)

1 INDICATIONS AND USAGE

LETYBO is an acetylcholine release inhibitor and a neuromuscular blocking agent indicated for the temporary improvement in the appearance of moderate to severe glabellar lines associated with corrugator and/or procerus muscle activity in adult patients. (1)

2 DOSAGE AND ADMINISTRATION

The recommended dose is 0.1 mL (4 Units) by intramuscular injection into each of five sites, for a total dose of 20 Units (2.2, 2.3)

3 DOSAGE FORMS AND STRENGTHS

For Injection: 50 Units or 100 Units freeze-dried powder in a single-dose vial (3)

4 CONTRAINDICATIONS

- Known hypersensitivity to any botulinum toxin preparation or to any of the components in the LETYBO formulation (4)
- Infection at the injection site (4)

5 WARNINGS AND PRECAUTIONS

- Spread of toxin effects; swallowing and breathing difficulties can lead to death. Seek immediate medical attention if respiratory, speech or swallowing difficulties occur. (5.1, 5.3, 5.7)
- Potency Units of LETYBO are not interchangeable with other preparations of botulinum toxin products. (5.2, 11)
- Potential serious adverse reactions after LETYBO injections for unapproved uses. (5.3)
- If a hypersensitivity reaction occurs, discontinue LETYBO and immediately initiate appropriate therapy. (5.4)
- Adverse event reports have been received involving the cardiovascular system, some with fatal outcomes. Use caution when administering to patients with pre-existing cardiovascular disease. (5.5)
- Concomitant neuromuscular disorder may exacerbate clinical effects of treatment. (5.6)
- Use with caution in patients with compromised respiratory function or dysphagia (5.7)

6 ADVERSE REACTIONS

The most common adverse reaction is headache (2%). (6.1)

To report SUSPECTED ADVERSE REACTIONS, contact HUGEL at 1‑888-674-5355 or FDA at 1-800-FDA-1088 or www.fda.gov/medwatch.

7 DRUG INTERACTIONS

Aminoglycoside antibiotics, anticholinergic agents, or any other agents that interfere with neuromuscular transmission may potentiate the effect of LETYBO; co-administer only with caution and close observation. (7)

FULL PRESCRIBING INFORMATION

WARNING: DISTANT SPREAD OF TOXIN EFFECT

The effects of all botulinum toxin products, including LETYBO, may spread from the area of injection to produce symptoms consistent with botulinum toxin effects. These symptoms have been reported hours to weeks after injection. Swallowing and breathing difficulties can be life threatening and there have been reports of death. LETYBO is not approved for the treatment of spasticity or any conditions other than glabellar lines [see Warnings and Precautions (5.1)].

1 INDICATIONS AND USAGE

LETYBO is indicated for the temporary improvement in the appearance of moderate to severe glabellar lines associated with corrugator and/or procerus muscle activity in adult patients.

2 DOSAGE AND ADMINISTRATION

2.1 Important Administration Instructions

The potency Units of LETYBO (letibotulinumtoxinA-wlbg) for injection are specific to the preparation and assay utilized. They are not interchangeable with other preparations of botulinum toxin products and, therefore, units of biological activity of LETYBO cannot be compared to nor converted into units of any other botulinum toxin products assessed with any other specific assay [see Warnings and Precautions (5.2) and Description (11)] .

LETYBO should be administered no more frequently than every three months. Consideration of the cumulative dose is necessary when treating adult patients with LETYBO for glabellar lines if other botulinum toxin products are or have been used to treat other indications approved for those products.

The safe and effective use of LETYBO depends upon proper storage of the product, selection of the correct dose, and proper reconstitution and administration techniques.LETYBO

After reconstitution, only use each LETYBO vial for one injection session and for only one patient. Discard any remaining solution in vial immediately after administration.

Reconstitution instructions are provided specifically for the 50 Unit and the 100 Unit vials (Table 1)

2.2 Recommended Dosage

The total recommended dose is 20 Units per treatment session divided into five equal intramuscular injections of 4 Units each (two injections in each corrugator muscle and one injection in the procerus muscle).

2.3 Preparation and Dilution Technique

LETYBO is supplied in a single-dose 50 or 100-Unit vial. Prior to intramuscular injection, reconstitute each freeze-dried vial of LETYBO with the required amount of sterile, preservative-free 0.9% Sodium Chloride Injection, USP to achieve a reconstituted solution at a concentration of 4 Units/0.1 mL (see Table 1).

Table 1: Dilution Instructions for LETYBO Vials (50 and 100 Units)
Vial | Amount of Diluent* Added | Resulting Dose Units per 0.1 mL
50 Units | 1.25 mL | 4 Units
100 Units | 2.5 mL | 4 Units

*Preservative-free 0.9% Sodium Chloride Injection, USP

Slowly inject the diluent into the vial. Discard the vial if a vacuum does not pull the diluent into the vial. Dispose of any unused diluent. Gently mix LETYBO with 0.9% sodium chloride injection, USP by rotating the vial.

Reconstituted LETYBO is clear and colorless, and free of particulate matter. Inspect visually the reconstituted LETYBO for particulate matter and discoloration prior to administration. Do not use if the solution is cloudy or discolored or contains flakes or particles.

Administer LETYBO within 24 hours after reconstitution. During this time period, store unused reconstituted LETYBO in a refrigerator between 2°C to 8°C (36°F to 46°F) in the original carton to protect from light. Do not freeze reconstituted LETYBO.

2.4 Administration

The upper eyelid margin position should be carefully examined for separation or weakness of the levator palpebrae superioris muscle. Evaluate the range of upper eyelid excursion while manually immobilizing the frontalis to assess degree of levator function and frontalis compensation.

In order to reduce the complication of eyelid ptosis the following steps should be taken:

Avoid injection near the levator palpebrae superioris, particularly in patients with larger brow depressor complexes.
Ensure the injected volume/dose is accurate and administer in a steady, controlled manner.
Lateral corrugator injections should be placed at least 1 cm above the bony supraorbital ridge.
Avoid injecting toxin closer than 1 centimeter above the central eyebrow.

Draw at least 0.5 mL of the properly reconstituted toxin into a sterile syringe and expel any air bubbles in the syringe barrel. Remove the needle used to reconstitute the product and attach a 30-31 gauge needle. Confirm the patency of the needle. Inject a dose of 0.1 mL (4 Units) intramuscularly into each of 5 sites, the inferomedial and superior middle of each corrugator and one in the mid-line of the procerus muscle for a total dose of 20 Units (see Figure 1).

3 DOSAGE FORMS AND STRENGTHS

For injection: 50 Units or 100 Units, freeze-dried powder in a single-dose vial for reconstitution with preservative-free 0.9% Sodium Chloride Injection, USP.

4 CONTRAINDICATIONS

LETYBO is contraindicated in:

- Patients with known hypersensitivity to any botulinum toxin preparation or to any of the components in the LETYBO formulation [see Warnings and Precautions (5.4)] .
- The presence of infection at the proposed injection site(s).

4.1 Known Hypersensitivity to Botulinum Toxin

BRANDNAME is contraindicated in individuals with known hypersensitivity to any botulinum toxin preparation or to any of the components in the formulation [see Warnings and Precautions (5.4)].

4.2 Infection at the Injection Site(s)

BRANDNAME is contraindicated in the presence of infection at the proposed injection site(s).

5 WARNINGS AND PRECAUTIONS

5.1 Spread of Toxin Effects

Postmarketing safety data from other approved botulinum toxins suggest that botulinum toxin effects may be observed beyond the site of local injection. The symptoms are consistent with the mechanism of action of botulinum toxin and may include asthenia, generalized muscle weakness, diplopia, ptosis, dysphagia, dysphonia, dysarthria, urinary incontinence, blurred vision and breathing difficulties. These symptoms have been reported hours to weeks after injection. Swallowing and breathing difficulties can be life threatening and there have been reports of death related to spread of toxin effects. In unapproved uses and approved indications, symptoms consistent with spread of toxin effects have been reported at doses comparable to or lower than the maximum recommended total dose [see Use in Specific Populations (8.4)] . LETYBO is not approved for any conditions other than glabellar lines. Patients or caregivers should be advised to seek immediate medical care if swallowing, speech or respiratory difficulties occur.

5.2 Lack of Interchangeability between Botulinum Toxin Products

The potency units of LETYBO are specific to the preparation and assay method utilized. They are not interchangeable with other preparations of botulinum toxin products and, therefore, units of biological activity of LETYBO cannot be compared to or converted into units of any other botulinum toxin products assessed with any other specific assay method [see Description (11)] .

5.3 Serious Adverse Reactions with Unapproved Use

Serious adverse reactions, including excessive weakness, dysphagia, and aspiration pneumonia, with some adverse reactions associated with fatal outcomes, have been reported in patients who received botulinum toxin injections for unapproved uses. In these cases, the adverse reactions may have resulted from the administration of botulinum toxin products to the site of injection and/or adjacent structures. In several of the cases, patients had preexisting dysphagia or other significant disabilities. There is insufficient information to identify factors associated with an increased risk for adverse reactions associated with the unapproved uses of botulinum toxin products.

5.4 Hypersensitivity Reactions

Serious and/or immediate hypersensitivity reactions have been reported for botulinum toxin products. These reactions include anaphylaxis, serum sickness, urticaria, soft tissue edema, and dyspnea. If such a reaction occurs, discontinue further injection of LETYBO and immediately institute appropriate medical therapy [see Contraindications (4)] .

5.5 Cardiovascular System Adverse Reactions

There have been reports following administration of botulinum toxins of adverse events involving the cardiovascular system, including arrhythmia and myocardial infarction, some with fatal outcomes. Some of these patients had risk factors including pre-existing cardiovascular disease. Use caution when administering to patients with pre-existing cardiovascular disease.

5.6 Increased Risk of Clinically Significant Effects with Pre-Existing Neuromuscular Disorders

Patients with neuromuscular disorders may be at increased risk of clinically significant effects including generalized muscle weakness, diplopia, ptosis, dysphonia, dysarthria, severe dysphagia, and respiratory compromise from typical doses of LETYBO. Monitor patients with peripheral motor neuropathic diseases, amyotrophic lateral sclerosis, or neuromuscular junction disorders (e.g., myasthenia gravis or Lambert-Eaton syndrome) for increased neuromuscular compromise following botulinum toxin treatment.

5.7 Dysphagia and Dyspnea

Treatment with botulinum toxin products, including LETYBO, can result in dysphagia and dyspnea including respiratory failure. These reactions can occur within hours to weeks after injection with botulinum toxin. Patients with preexisting dysphagia and dyspnea may be more susceptible to these complications. In most cases, this has been a consequence of weakening of muscles in the area of injection that are involved in breathing or oropharyngeal muscles that control swallowing or breathing

Deaths as a complication of severe dysphagia have been reported after treatment with botulinum toxin products. Dysphagia may persist for several months. Patients treated with botulinum toxin products, including LETYBO, may require immediate medical attention should they develop problems with swallowing, speech, or breathing. These reactions can occur within hours to weeks after injection with botulinum toxin [see Warnings and Precautions (5.1)] .

5.8 Pre-existing Conditions at the Injection Site

Use caution when LETYBO treatment is used in the presence of inflammation at the proposed injection site(s) or when excessive weakness or atrophy is present in the target muscle(s).

Use caution when LETYBO treatment is used in patients who have marked facial asymmetry, with surgical alterations to the facial anatomy, pre-existing eyelid or eyebrow ptosis, when excessive weakness or atrophy is present in the target muscles, excessive dermatochalasis, deep dermal scarring, thick sebaceous skin (e.g., the inability to substantially lessen glabellar lines even by physically spreading them apart).

5.9 Ophthalmic Adverse Reactions in Patients Treated with Botulinum Toxin Products

Dry eye has been reported with the use of botulinum toxin products in the treatment of glabellar lines. Reduced tear production, reduced blinking, and corneal disorders may occur with use of botulinum toxins, including LETYBO. If symptoms of dry eye (e.g., eye irritation, photophobia or visual changes) persist, consider referring patient to an ophthalmologist [see Warnings and Precautions (5.1)] .

5.10 Human Albumin and Transmission of Viral Diseases

This product contains albumin, a derivative of human blood. Based on effective donor screening and product manufacturing processes, it carries a remote risk for transmission of viral diseases and variant Creutzfeldt-Jakob disease (CJD). There is a theoretical risk for transmission of Creutzfeldt-Jakob disease (CJD), which would also be considered remote. No cases of transmission of viral diseases or CJD or vCJD have ever been identified for licensed albumin or albumin contained in other licensed products.

6 ADVERSE REACTIONS

The following serious adverse reactions are discussed in greater detail in other sections of the labeling:

- Spread of Toxin Effects [see Warnings and Precautions (5.1)]
- Hypersensitivity Reactions [see Contraindications (4) and Warnings and Precautions (5.4)]
- Cardiovascular System Adverse Reactions [see Warnings and Precautions (5.5)]
- Increased Neuromuscular Compromise in Patients with Pre-Existing Neuromuscular Disorders [see Warnings and Precautions (5.6)]
- Dysphagia and Dyspnea [see Warnings and Precautions (5.7)]
- Ophthalmic Adverse Reactions in Patients Treated for Glabellar Lines [see Warnings and Precautions (5.9)]

6.1 Clinical Trials Experience

Because clinical trials are conducted under widely varying conditions, the adverse reaction rates observed in the clinical trials of a drug cannot be directly compared to rates in the clinical trials of another drug and may not reflect the rates observed in clinical practice.

In the three randomized, placebo-controlled, Phase 3 clinical trials that assess the use of LETYBO for the temporary improvement in the appearance of moderate to severe glabellar lines (BLESS I, II and III), 911 out of the 955 subjects who received a single dose treatment of 20 Units LETYBO and 310 out of the 317 subjects who received a single dose of placebo were included in safety analyses [see Clinical Studies (14)] .

Table 2 lists the adverse reactions reported in more than one subject in the LETYBO group compared to the placebo in the placebo-controlled trials. Most adverse reactions occur within the first week following injection of LETYBO and while generally transient, may have a duration of several months or longer.

Table 2: Adverse Reactions Reported in More Than One Subject in the LETYBO Group Compared to the Placebo Group in BLESS I, II and III
Adverse Reaction | Treatment
Adverse Reaction | LETYBO; BLESS I, II, III; N=911; n (%) | PLACEBO; BLESS I, II, III; N=310; n (%)
Headache* | 17 (2%) | 2 (1%)
Brow ptosis** | 3 (<1%) | 0
Eyelid ptosis | 3 (<1%) | 0
Blepharospasm | 2 (<1%) | 0

* Includes headache, head discomfort, migraine, and procedural headache.

** Includes brow ptosis and brow heaviness.

The most frequently reported injection site reactions included administrative site swelling, facial pain, folliculitis, periorbital hematoma; and injection site bruising, reaction, pain, hematoma, nodule, pruritus, and mass.

BLESS I, II and III also included an open label, extension part with LETYBO. The extension allowed subjects who had completed the double-blind portion of the trials to receive up to 3 additional elective LETYBO 20-Unit treatments for moderate to severe glabellar lines over a 48-week period. Treatments were separated by at least a 3-month period. Of the 1,129 subjects enrolled in the open label extension part of the trials, the median number of treatments was 3. The adverse reaction profile was comparable to that reported in the randomized, single dose, double blind part of the trials.

Headache was the most common adverse reaction, reported in 2% of subjects, followed by injection site reactions (1%) [including contusion/bruising, administration site swelling, facial pain, periorbital hematoma, skin swelling; and injection site reaction, bruising, hematoma, mass, and nodule] and eyelid ptosis in 0.5% of subjects. The incidence of these adverse reactions did not increase with multiple re-treatments.

6.2 Immunogenicity

As with all therapeutic proteins, there is a potential for immunogenicity. The detection of antibody formation is highly dependent on the sensitivity and specificity of the assay. Additionally, the observed incidence of antibody (including neutralizing antibody) positivity in an assay may be influenced by several factors including assay methodology, sample handling, timing of sample collection, concomitant medications, and underlying disease. For these reasons, comparison of the incidence of antibodies to letibotulinumtoxinA-wlbg in the studies described below with the incidence of antibodies in other studies or to other products may be misleading.

Treatment with botulinum toxins may result in the formation of antibodies that may reduce the effectiveness of subsequent treatments by inactivating biological activity of the toxin. Among 1,195 subjects treated with letibotulinumtoxinA-wlbg, four subjects (0.3%) developed antibodies to letibotulinumtoxinA-wlbg following treatment with LETYBO. In the selected anti-drug antibodies positive samples that were further tested, there were no neutralizing anti-drug antibodies detected.

7 DRUG INTERACTIONS

No drug interaction studies have been conducted with LETYBO. Certain drugs may potentiate the effects of LETYBO which may result in excessive neuromuscular weakness and heighten systemic anticholinergic effects. Use caution with concurrent use of LETYBO with the following products and monitor closely for excessive neuromuscular weakness:

- Aminoglycosides or other agents interfering with neuromuscular transmission
- Anticholinergic drugs
- Botulinum neurotoxin products administered as the same time or within several months of LETYBO
- Muscle relaxants administered before or after administration of LETYBO

8 USE IN SPECIFIC POPULATIONS

8.1 Pregnancy

Risk Summary

Available data from case reports with LETYBO use in pregnant women are insufficient to identify a drug-associated risk of major birth defects, miscarriage, or other adverse maternal or fetal outcomes. Systemic exposure following intramuscular injection of letibotulinumtoxinA-wlbg was not assessed [see Clinical Pharmacology (12.3)] . In an animal reproduction study, intramuscular administration of letibotulinumtoxinA‑wlbg to rats during pregnancy resulted in adverse effects on fetal growth (decreased fetal body weight and skeletal ossification) at maternally toxic doses 3 times the maximum recommended human dose (MRHD) (see Data).

The background risk of major birth defects and miscarriage for the indicated population is unknown. All pregnancies have a background risk of birth defect, loss or other adverse outcomes. In the U.S. general population, the estimated background risk of major birth defects and miscarriage in clinically recognized pregnancies is 2 to 4% and 15 to 20%, respectively.

Data

Animal Data

An embryofetal development study was conducted in rats with letibotulinumtoxinA-wlbg. For comparison of animal to human doses based on a body weight comparison, the MRHD is set at 20 Units/subject (0.34 Units/kg for an average 60 kg subject). Administration to pregnant rats once daily during organogenesis (gestation days 5 to 16) caused decreased fetal body weight and decreased fetal skeletal ossification at doses ≥1 Unit/kg (3 times the MRHD. These treatment related effects were associated with maternal toxicity.

8.2 Lactation

Risk Summary

There are no data regarding the presence of letibotulinumtoxinA-wlbg in human or animal milk, its effects on the breastfed infant, or the effects on milk production. Systemic exposure following intramuscular injection of letibotulinumtoxinA-wlbg was not assessed [see Clinical Pharmacology (12.3)] .The developmental and health benefits of breastfeeding should be considered along with the mother’s clinical need for LETYBO and any potential adverse effects on the breastfed infant from LETYBO or from the underlying maternal condition.

8.4 Pediatric Use

The safety and effectiveness of LETYBO in pediatric patients have not been established.

8.5 Geriatric Use

The 3 clinical trials of LETYBO included 148 subjects age 65 and greater. Although no clinically meaningful differences in safety or efficacy were observed between older and younger subjects, clinical studies of LETYBO did not include sufficient numbers of subjects aged 65 and over to determine whether they respond differently from younger subjects.

10 OVERDOSAGE

Excessive doses of LETYBO may be expected to produce neuromuscular weakness with a variety of symptoms. Respiratory support may be required where excessive doses cause paralysis of the respiratory muscles. Symptoms of overdose are likely not to be present immediately following injection. Should accidental injection or oral ingestion occur, or overdose be suspected, the person should be medically supervised for several weeks for signs and symptoms of systemic muscular weakness or paralysis.

In the event of overdose, antitoxin raised against botulinum toxin is available from the Centers for Disease Control and Prevention (CDC) in Atlanta, GA. However, the antitoxin will not reverse any botulinum toxin-induced effects already apparent by the time of antitoxin administration. In the event of suspected or actual cases of botulinum toxin poisoning, please contact your local or state Health Department to process a request for antitoxin through the CDC. If you do not receive a response within 30 minutes, please contact the CDC directly at 1-770-488-7100.

11 DESCRIPTION

LetibotulinumtoxinA-wlbg is an acetylcholine release inhibitor and a neuromuscular blocking agent. LetibotulinumtoxinA-wlbg is a 900 kDa botulinum toxin type A, produced from fermentation of Clostridium botulinum.

LETYBO (letibotulinumtoxinA-wlbg) for injection is supplied as a sterile, preservative-free, white, freeze-dried powder in a single-dose vial for intramuscular use after reconstitution. Each vial contains either 50 Units of letibotulinumtoxinA-wlbg, albumin human (0.25 mg) and sodium chloride (0.45 mg); or 100 Units of letibotulinumtoxinA-wlbg, albumin human (0.5 mg) and sodium chloride (0.9 mg).

12 CLINICAL PHARMACOLOGY

12.1 Mechanism of Action

LETYBO blocks cholinergic transmission at the neuromuscular junction by inhibiting the release of acetylcholine. When injected intramuscularly at therapeutic doses, LETYBO is internalized into the nerve terminal, translocates into the neuronal cytosol where it cleaves SNAP25, a protein necessary for synaptic membrane docking and subsequent release of acetylcholine which produces a dose dependent decrease of muscle function. Recovery of muscle function is gradual due to degradation of the neurotoxin and formation of axonal sprouts. Muscle reinnervation occurs, leading to a slow reversal of the pharmacological effects of LETYBO.

12.2 Pharmacodynamics

No formal pharmacodynamic studies have been conducted with LETYBO.

12.3 Pharmacokinetics

Using currently available analytical technology, it is not possible to detect LETYBO in the peripheral blood following intramuscular injection at the recommended doses.

13 NONCLINICAL TOXICOLOGY

13.1 Carcinogenesis, Mutagenesis, Impairment of Fertility

Animal studies have not been conducted to evaluate the carcinogenic, mutagenic, or impairment of fertility potential of letibotulinumtoxinA-wlbg.

14 CLINICAL STUDIES

Three randomized, multi-center, double-blind, placebo-controlled trials (BLESS I [NCT02677298], BLESS II [NCT02677805] and BLESS III [NCT03985982]) of identical design were conducted to evaluate LETYBO for use in the temporary improvement of the appearance of moderate to severe glabellar facial lines. These trials enrolled 1,276 subjects, randomized 3 to 1 to a single treatment with LETYBO (n=957) or placebo (n=319). Of the 1,276 enrolled subjects, 1,271 were included in the full analysis set (FAS) evaluable for efficacy with LETYBO (n=954) and placebo (n=317).

The trials enrolled healthy adults (ranging in age from 19 to 75) with glabellar lines of at least moderate severity at maximum frown and excluded subjects who had ptosis, deep dermal scarring or an inability to substantially lessen glabellar lines even by physically spreading the glabellar lines apart. The mean age was 50 years with 152 subjects (12%) ≥65 years of age. Most of the subjects were women (91%) and White (91%). Injection volume was 0.1 mL/injection site, for a dose/injection site in the active treatment groups of 4 Units. Subjects were injected intramuscularly at 5 sites, 1 in the procerus muscle and 2 in each corrugator supercilii muscle, for a total dose in the active treatment groups of 20 Units.

The primary efficacy endpoint was measured at Week 4 and was defined as the proportion of subjects achieving a score of 0 or 1 and an improvement of at least 2 points from baseline at maximum frown, as assessed independently by both the investigator and the subject using the Glabellar Line Scale (GLS). The GLS is a 4-point grading scale (0=none, 1=mild, 2=moderate, 3=severe). The results of these 3 efficacy trials are presented in Table 3.

Table 3: Percentage of Subjects with Moderate to Severe Glabellar Lines Achieving a Score of 0 or 1 and an Improvement of At Least 2 Points from Baseline to Week 4 at Maximum Frown on the Investigator and Subject Assessment of Glabellar Line Severity (Full Analysis Set) in Trials BLESS I, II, and III
 | BLESS I |  | BLESS II |  | BLESS III
 | LETYBO (N = 528) | Placebo (N = 175) | LETYBO (N = 160) | Placebo (N = 53) | LETYBO (N = 266) | Placebo (N = 89)
Treatment Success*
Multi-component Assessment n (%) | 246 (47%) | 0 (0%) | 78 (49%) | 1 (2%) | 172 (65%) | 0 (0%)
Treatment Difference and 95% Confidence Interval** | 47% (43%, 51%) |  | 45% (36%, 54%) |  | 65% (59%, 71%)
Individual Components
Investigator Assessment; n (%) | 348 (66%) | 1 (1%) | 120 (75%) | 1 (2%) | 209 (79%) | 1 (1%)
Subject Assessment; n (%) | 290 (55%) | 0 (0%) | 83 (52%) | 1 (2%) | 183 (69%) | 0 (0%)
* A score of 0 or 1 (none or mild) and an improvement of at least 2 points from baseline at maximum frown concurrently on both the investigator’s and subject’s assessments
** Based on the Mantel-Haenszel method

16 HOW SUPPLIED/STORAGE AND HANDLING

How Supplied

LETYBO (letibotulinumtoxinA-wlbg) for injection is a sterile, white, freeze-dried powder supplied in a single-dose vial in the following sizes:

Carton containing one 50 Units/vial (NDC 81165-050-01)

Carton containing one 100 Units/vial (NDC 81165-100-01)

Storage and Handling

Unopened LETYBO vials should be stored in a refrigerator between 2°C to 8°C (36°F to 46°F) in the original carton to protect from light.

Do not freeze.

17 PATIENT COUNSELING INFORMATION

Advise the patient to read the FDA-approved patient labeling (Medication Guide).

Swallowing, Speaking or Breathing Difficulties, or other Unusual Symptoms

Advise patients or caregivers to seek immediate medical care if swallowing, speech, or respiratory disorders arise or existing symptoms worsen [see Warnings and Precautions (5.1, 5.6)].

Ability to Operate Machinery or Vehicles

Advise patients that if loss of strength, muscle weakness, blurred vision or drooping eyelids occur, they should avoid driving a car or engaging in other potentially hazardous activities [see Warnings and Precautions (5.1)].

Ophthalmic Adverse Reaction

Inform patients that LETYBO injection may cause eye dryness. Advise patients to report symptoms of eye dryness (e.g., eye pain, eye irritation, photosensitivity or changes in vision) to their healthcare provider [see Warnings and Precautions (5.9)].

Manufactured by:

Hugel, Inc.

23, Geodudanji 1-gil, Dongnae-myeon, Chuncheon, 24398 Korea

U.S. License Number 2237

© 02/2024

All trademarks are the property of their respective owners

MEDICATION GUIDE

LETYBO (le tye boe)

(letibotulinumtoxinA-wlbg)

for injection, for intramuscular use

What is the most important information I should know about LETYBO?

LETYBO may cause serious side effects that can be life threatening. Call your healthcare provider or get medical help right away if you have any of these problems after treatment with LETYBO:

- Problems swallowing, speaking, or breathing. These problems can happen hours, days, or weeks after an injection of LETYBO if the muscles that you use to breathe and swallow become weak after the injection. Death can happen as a complication if you have severe problems with swallowing or breathing after treatment with LETYBO.
- People with certain breathing problems may need to use muscles in their neck to help them breathe. These people may be at greater risk for serious breathing problems with LETYBO.
  - Swallowing problems may last for several months. People who cannot swallow well may need a feeding tube to receive food and water. If swallowing problems are severe, food or liquids may go into your lungs. People who already have swallowing or breathing problems before receiving LETYBO have the highest risk of getting these problems.
- Spread of toxin effects. In some cases, the effect of botulinum toxin may affect areas of the body away from the injection site and cause symptoms of a serious condition called botulism. The symptoms of botulism include:
- loss of strength and muscle weakness all over the body
- double vision, blurred vision, and drooping eyelids
- hoarseness or change or loss of voice
- trouble saying words clearly
- loss of bladder control
- trouble breathing
- trouble swallowing

These symptoms can happen hours, days, or weeks after you receive an injection of LETYBO.

These problems could make it unsafe for you to drive a car or do other dangerous activities. See “What should I avoid while receiving LETYBO?”

What is LETYBO?

LETYBO is a prescription medicine for adults that is injected into muscles to temporarily improve the look of moderate to severe frown lines between the eyebrows (glabellar lines).

It is not known if LETYBO is safe and effective for use in children.

Do not receive LETYBO if you:

- are allergic to LETYBO or any of the ingredients in LETYBO. See the end of this Medication Guide for a list of ingredients in LETYBO.
- had an allergic reaction to any other botulinum toxin product such as rimabotulinumtoxinB (MYOBLOC), onabotulinumtoxinA (BOTOX, BOTOX COSMETIC), abobotulinumtoxinA (DYSPORT), incobotulinumtoxinA (XEOMIN), prabotulinumtoxinA-xvfs (JEUVEAU), or daxibotulinumtoxinA-lanm (DAXXIFY).
- have a skin infection at the planned injection site.

Before receiving LETYBO, tell your healthcare provider about all of your medical conditions, including if you:

- have a disease that affects your muscles and nerves (such as amyotrophic lateral sclerosis [ALS or Lou Gehrig’s disease], myasthenia gravis or Lambert-Easton syndrome). See “What is the most important information I should know about LETYBO?”
- had any side effect from any botulinum toxin product in the past
- have or have had a breathing problem, such as asthma or emphysema
- have or have had swallowing problems
- have or have had bleeding problems
- have or have had heart problems
- plan to have surgery
- have weakness of your forehead muscles, such as trouble raising your eyebrows
- have drooping eyelids
- have had surgery on your face
- have had dry eyes with the use of botulinum toxin products in the past
- are pregnant or plan to become pregnant. It is not known if LETYBO can harm your unborn baby.
- are breastfeeding or plan to breastfeed. It is not known if LETYBO passes into breast milk. Talk to your healthcare provider about the best way to feed your baby during treatment with LETYBO.

Tell your healthcare provider about all the medicines you take, including prescription and over-the-counter medicines, vitamins, and herbal supplements.

Using LETYBO with certain other medicines may cause serious side effects. Do not start any new medicines until you have told your healthcare provider that you have received LETYBO in the past.

Especially tell your healthcare provider if you:

- have received any other botulinum toxin product in the last several months.
- have received injections of botulinum toxin, such as prabotulinumtoxinA-xvfs (JEUVEAU), onabotulinumtoxinA (BOTOX, BOTOX COSMETIC), rimabotulinumtoxinB (MYOBLOC), abobotulinumtoxinA (DYSPORT), incobotulinumtoxinA (XEOMIN), or daxibotulinumtoxinA-lanm (DAXXIFY) in the past. Be sure your healthcare provider knows exactly which product you received.

Know the medicines you take. Keep a list of your medicines with you to show your healthcare provider and pharmacist each time you get a new medicine.

How will I receive LETYBO?

- LETYBO is an injection that your healthcare provider will give you.
- LETYBO is injected into your affected muscles.
- LETYBO should not be received more than 1 time every 3 months.
- Your healthcare provider may change your dose of LETYBO, until you and your healthcare provider find the best dose for you.
- Your healthcare provider will tell you how often you will receive your dose of LETYBO injections.

What should I avoid while receiving LETYBO?

LETYBO may cause loss of strength or general muscle weakness, blurred vision, or drooping eyelids within hours to weeks of receiving LETYBO. If this happens, do not drive a car, operate machinery, or do other dangerous activities. See “What is the most important information I should know about LETYBO?”

What are the possible side effects of LETYBO?

LETYBO may cause serious side effects, including:

- See “What is the most important information I should know about LETYBO?"
- Allergic reactions. Symptoms of an allergic reaction to LETYBO may include: itching, rash, hives, wheezing, trouble breathing, or you may become dizzy or faint. Tell your healthcare provider or get emergency medical help right away if you develop wheezing or trouble breathing, or if you feel dizzy or faint.
- Heart problems. Irregular heartbeat and heart attack that have caused death, have happened in some people who received botulinum toxin products.
- Eye problems. Dry eye, reduced blinking, and corneal problems have happened in some people who receive LETYBO. Tell your healthcare provider if you develop eye pain or irritation, sensitivity to light, or changes in your vision.

The most common side effect of LETYBO was headache.

These are not all of the possible side effects of LETYBO.

Call your doctor for medical advice about side effects. You may report side effects to FDA at 1-800-FDA-1088.

You may also report side effect to Hugel, Inc. at 1-877-390-2906.

General information about the safe and effective use of LETYBO.

Medicines are sometime prescribed for purposes other than those listed in a Medication Guide. You can ask your healthcare provider or pharmacist for information about LETYBO that is written for healthcare professionals.

What are the ingredients in LETYBO?

Active ingredient: letibotulinumtoxinA-wlbg

Inactive ingredients: albumin human and sodium chloride

Manufactured by: Hugel, Inc., 23, Geodudanji 1-gil, Dongnae-myeon, Chuncheon, 24398 Korea

U.S. License No. 2237

© 02/2024

This Medication Guide has been approved by the U.S. Food and Drug Administration

Issued: 02/2024

PRINCIPAL DISPLAY PANEL - 50 Units/vial

NDC 81165-050-01

PRINCIPAL DISPLAY PANEL - 100 Units/vial

NDC 81165-100-01